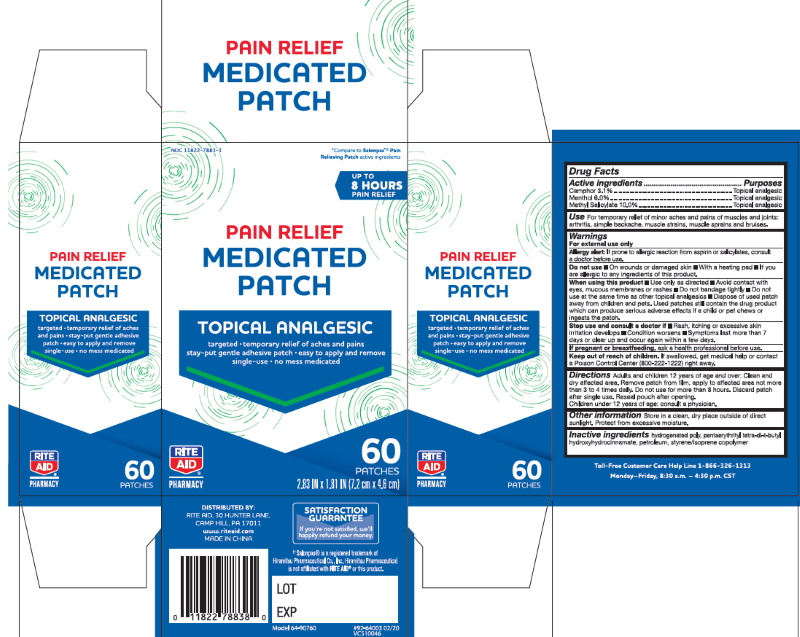 DRUG LABEL: Pain Relief Medicated
NDC: 11822-7883 | Form: PATCH
Manufacturer: RITE AID CORPORATION
Category: otc | Type: HUMAN OTC DRUG LABEL
Date: 20250116

ACTIVE INGREDIENTS: CAMPHOR (SYNTHETIC) 3.1 g/100 g; MENTHOL 6 g/100 g; METHYL SALICYLATE 10 g/100 g
INACTIVE INGREDIENTS: HYDROGENATED POLY(C6-14 OLEFIN; 2 CST); PENTAERYTHRITOL TETRAKIS(3-(3,5-DI-TERT-BUTYL-4-HYDROXYPHENYL)PROPIONATE); LIQUID PETROLEUM; STYRENE

Pain Relieving Patches

ACTIVE INGREDIENT

Active Ingredient | Purpose
Camphor 3.1% | Topical Analgesic
Menthol 6.0% | Topical Analgesic
Methyl Salicylate 10.0% | Topical Analgesic

INACTIVE INGREDIENT

hydrogenated poly, pentaerythrityl tetra-di-t-butyl hydroxyhydrocinnamate, petroleum, styrene/isoprene copolymer

KEEP OUT OF REACH OF CHILDREN

If swallowed, get medical help or contact a Poison Control Center (800-222-1222) right away.

INDICATIONS & USAGE

For temporary relief of minor aches and pains of muscles and joins: arthritis, simple backache, muscle strains, muscle sprains and bruises.

WARNINGS

For External Use Only

Allergy Alert:If prone to allergic reactions from aspirine or salicytates, consult a doctor before use.

DOSAGE & ADMINISTRATION

Adults and children 12 years of age and over:

Clean and dry affected area. Remove patch from film, apply to affected area not more than 3-4 times a day.

Do not use for more than 8 hours.

Discard patch after use.

Reseal pouch after opening.

Children under 12 years of age, consult a physician.

If pregnant or breastfeeding

ask a health professional before use.

PURPOSE

Topical Analgesic

When using this product:

■ Use only as directed ■ Avoid contact with eyes, mucous membranes or rashes ■ Do not bandage tightly ■ Do not use at the same time as other topical analgesics ■ Dispose of used patch away from children and pets. Used patches still contain the drug product which can produce serious adverse effects if a child or pet chews or ingests the patch.

Do not use

- On wounds or damaged skin
- With a heating pad
- If you are allergic to any ingredients in this product.

Stop use and consult a doctor

- If rash, itching or excessive skin irritation develops
- If condition worsens
- If symptoms last more than 7 days or clear up and occur again in a few days.

Storage and Care

Store in a clean, dry place outside of direct sunlight. Protect from excessive moisture.

Pain Relieving Path

DIST. BY
RITE AID Co.
30 Hunter Lane
Camp Hill, PA 17011
www.riteaid.com

TOLL-FREE CUSTOMER CARE HELP LINE Mon–Fri, 8:30 am–4:30 pm CST 866-326-1313